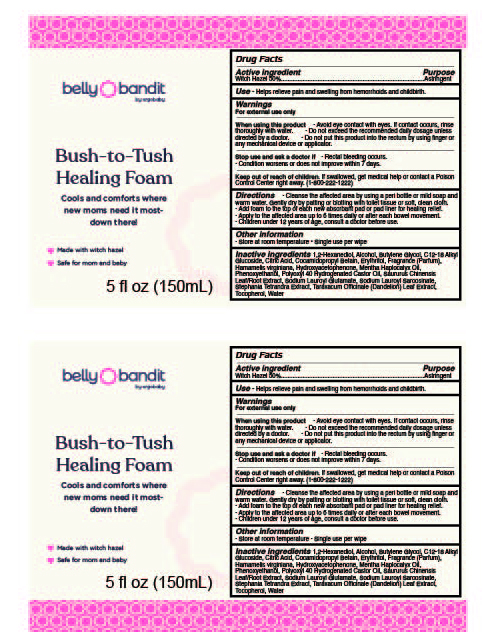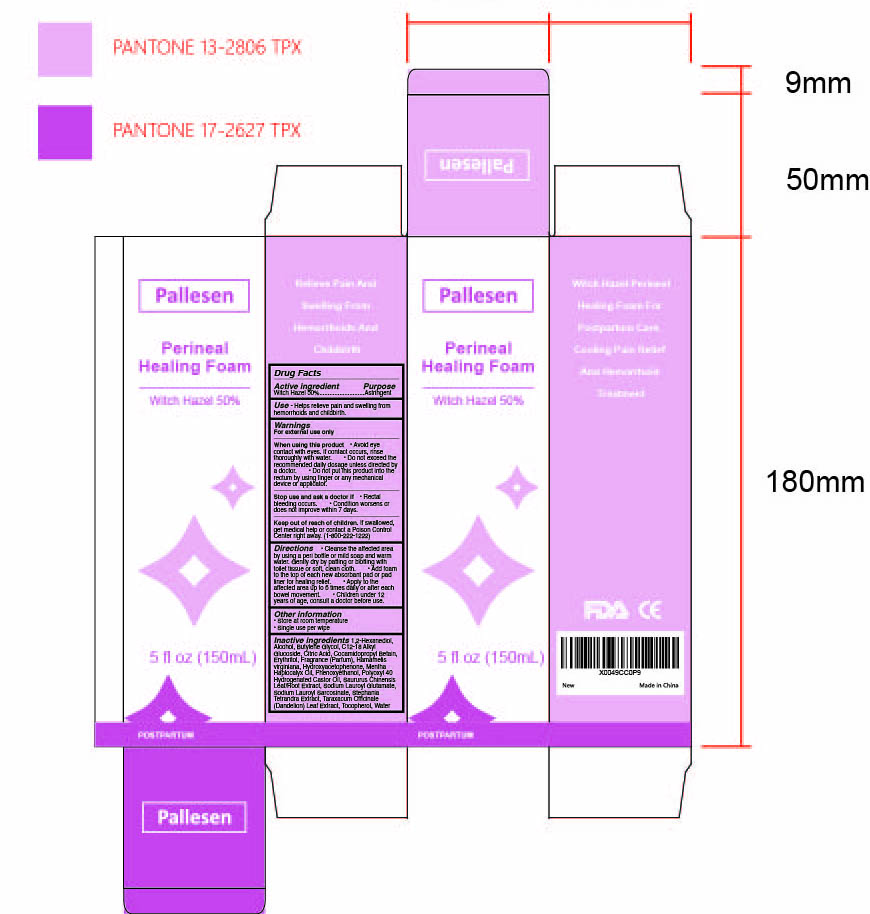 DRUG LABEL: Bush to Tush Healing Perineal Foam
NDC: 84576-001 | Form: AEROSOL, FOAM
Manufacturer: Ergobaby Carriers, Inc
Category: otc | Type: HUMAN OTC DRUG LABEL
Date: 20240722

ACTIVE INGREDIENTS: WITCH HAZEL 50 g/100 mL
INACTIVE INGREDIENTS: CITRIC ACID MONOHYDRATE; WATER; TOCOPHEROL; POLYOXYL 40 HYDROGENATED CASTOR OIL; STEPHANIA TETRANDRA ROOT; PHENOXYETHANOL; MENTHA CANADENSIS WHOLE; COCAMIDOPROPYL BETAINE; HYDROXYACETOPHENONE; SAURURUS CHINENSIS WHOLE; LAURYL GLUCOSIDE; SODIUM LAUROYL GLUTAMATE; ERYTHRITOL; ALCOHOL; TARAXACUM OFFICINALE; 1,2-HEXANEDIOL; BUTYLENE GLYCOL; SODIUM LAUROYL SARCOSINATE

Directions

• Cleanse the affected area by using a peri bottle or mild soap and
warm water. Gently dry by patting or blotting with toilet tissue or soft, clean cloth.
• Add foam to the top of each new absorbant pad or pad liner for healing relief.
• Apply to the affected area up to 6 times daily or after each bowel movement.
• Children under 12 years of age, consult a doctor before use.

WARNINGS

For external use only
When using this product • Avoid eye contact with eyes. If contact occurs, rinse
thoroughly with water. • Do not exceed the recommended daily dosage unless
directed by a doctor. • Do not put this product into the rectum by using finger or
any mechanical device or applicator.

INACTIVE INGREDIENT

1,2-Hexanediol, Alcohol, Butylene Glycol, C12-18 Alkyl
Glucoside, Citric Acid, Cocamidopropyl Betain, Erythritol, Fragrance (Parfum),
Hamamelis virginiana, Hydroxyacetophenone, Mentha Haplocalyx Oil,
Phenoxyethanol, Polyoxyl 40 Hydrogenated Castor Oil, Saururus Chinensis
Leaf/Root Extract, Sodium Lauroyl Glutamate, Sodium Lauroyl Sarcosinate,
Stephania Tetrandra Extract, Taraxacum Officinale (Dandelion) Leaf Extract,
Tocopherol, Water

INDICATIONS AND USAGE

Helps relieve pain and swelling from hemorrhoids and childbirth.

KEEP OUT OF REACH OF CHILDREN

If swallowed, get medical help or contact a Poison
Control Center right away. (1-800-222-1222)

Stop use and ask a doctor if • Rectal bleeding occurs.
• Condition worsens or does not improve within 7 days.

ACTIVE INGREDIENT

Witch Hazel 50%

PURPOSE

Astringent

OTHER SAFETY INFORMATION

• Store at room temperature • Single use per wipe